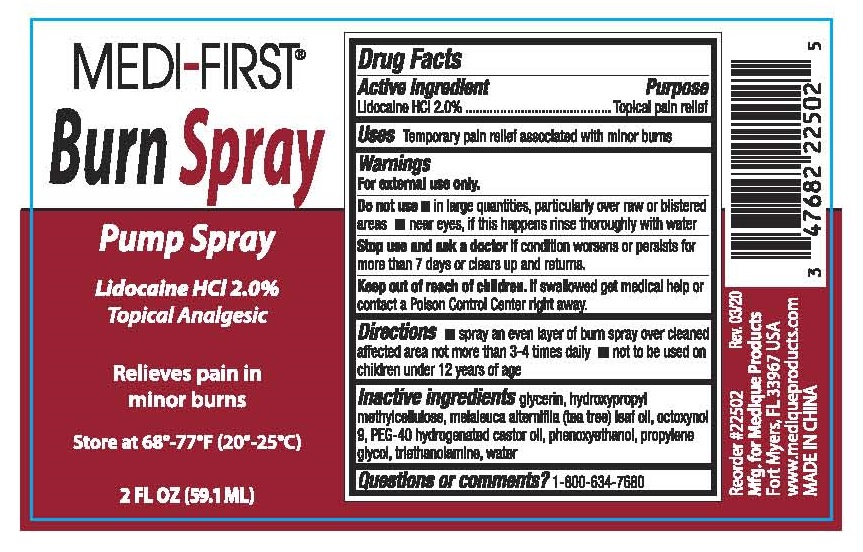 DRUG LABEL: MEDI-FIRST Topical Analgesic
NDC: 78495-142 | Form: SPRAY
Manufacturer: Ultra Distributors Inc
Category: otc | Type: HUMAN OTC DRUG LABEL
Date: 20250407

ACTIVE INGREDIENTS: LIDOCAINE HYDROCHLORIDE 20 mg/1 mL
INACTIVE INGREDIENTS: WATER; GLYCERIN; OCTOXYNOL-9; PHENOXYETHANOL; PROPYLENE GLYCOL; TROLAMINE; HYPROMELLOSES; TEA TREE OIL; POLYOXYL 40 HYDROGENATED CASTOR OIL

78495-142

Active ingredient

Lidocaine HCI 2.0%

Purpose

Topical pain relief

Uses

Temporary pain relief associated with minor burns

Warnings

For external use only.

Do not use

- in large quantities, particularly over raw or blistered areas
- near eyes, if this happens rinse thoroughly with water

Stop use and ask a doctor

if condition worsens or persists for more than 7 days or clears up and returns.

Keep out of reach of children

If swallowed, get medical help or contact a Poison Control Center right away.

Directions

- spray an even layer of burn spray over cleaned affected area not more than 3-4 times daily
- not to be used on Children under 12 years of age

Inactive ingredients

glycerin, hydroxypropyl methylcellulose, melaleuca alterniflia (tea tree) leaf oil, octoxynol 9,PEG-40 hydrogenated castor oil, phenoxyethanol, propylene glycol, triethanolamine, water

Questions or comments?

1-800-634-7680

Topical Analgesic

Relieves pain in minor burns

Store at 68°-77°F (20°-25°C)